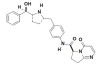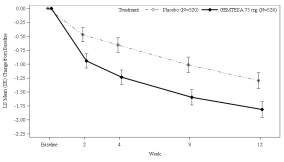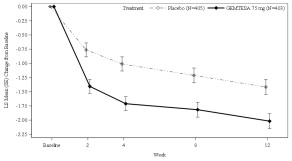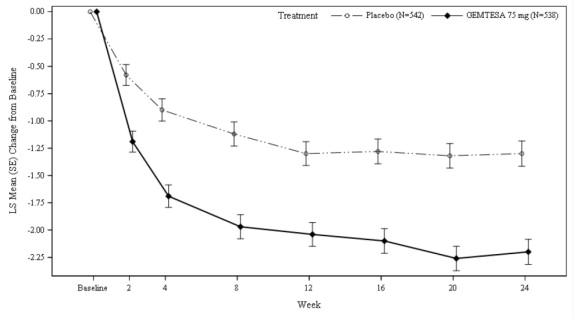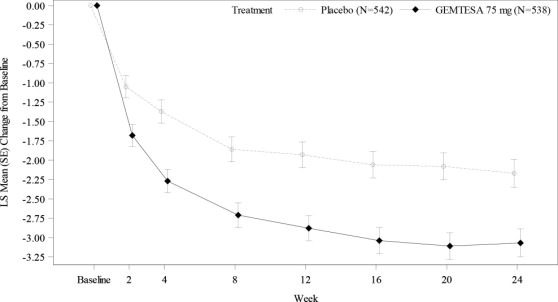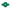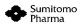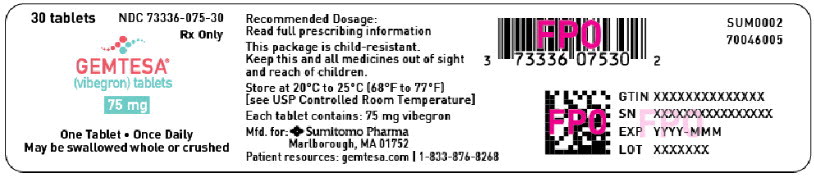 DRUG LABEL: GEMTESA

NDC: 73336-075 | Form: TABLET, FILM COATED
Manufacturer: Sumitomo Pharma America, Inc.

Category: prescription | Type: HUMAN PRESCRIPTION DRUG LABEL
Date: 20250401

ACTIVE INGREDIENTS: vibegron
 75 mg/1 1
INACTIVE INGREDIENTS: mannitol; microcrystalline cellulose; croscarmellose sodium; HYDROXYPROPYL CELLULOSE, UNSPECIFIED; magnesium stearate; FD&C BLUE NO. 2 ALUMINUM LAKE; lactose monohydrate; hypromellose, unspecified; FERRIC OXIDE YELLOW; titanium dioxide; triacetin

HIGHLIGHTS OF PRESCRIBING INFORMATION

These highlights do not include all the information needed to use GEMTESA® safely and effectively. See full prescribing information for GEMTESA.
GEMTESA (vibegron) tablets, for oral use
Initial U.S. Approval: 2020

RECENT MAJOR CHANGES

Indications and Usage, Overactive Bladder in Adult Males with Benign Prostatic Hyperplasia (1.2) | 12/2024
Contraindications (4) | 10/2024
Warnings and Precautions, Angioedema (5.2) | 10/2024

1 INDICATIONS AND USAGE

GEMTESA is a beta-3 adrenergic agonist indicated for the treatment of:

- overactive bladder (OAB) with symptoms of urge urinary incontinence, urgency, and urinary frequency in adults. (1.1)
- overactive bladder (OAB) with symptoms of urge urinary incontinence, urgency, and urinary frequency in adult males on pharmacological therapy for benign prostatic hyperplasia (BPH). (1.2)

2 DOSAGE AND ADMINISTRATION

- The recommended dose is one 75 mg tablet orally once daily. (2.1)
- Swallow tablet whole with water. (2.1)
- Tablet may be crushed and mixed with applesauce. (2.1)

3 DOSAGE FORMS AND STRENGTHS

Tablets: 75 mg (3)

4 CONTRAINDICATIONS

Do not use if prior hypersensitivity reaction to vibegron or any components of the product. (4)

5 WARNINGS AND PRECAUTIONS

Urinary Retention: Monitor for urinary retention, especially in patients with bladder outlet obstruction and also in patients taking muscarinic antagonist medications for OAB, in whom the risk of urinary retention may be greater. If urinary retention develops, discontinue GEMTESA. (5.1)

Angioedema: Angioedema of the face and/or larynx has been reported with GEMTESA. (5.2)

6 ADVERSE REACTIONS

Most common adverse reactions (≥2%) reported with GEMTESA were headache, urinary tract infection, nasopharyngitis, diarrhea, nausea, and upper respiratory tract infection. (6.1)

To report SUSPECTED ADVERSE REACTIONS, contact Sumitomo Pharma America, Inc. at 1-833-876-8268 or FDA at 1-800-FDA-1088 or www.fda.gov/medwatch.

7 DRUG INTERACTIONS

Digoxin: Measure serum digoxin concentrations before initiating GEMTESA. Monitor serum digoxin concentrations to titrate digoxin dose to desired clinical effect. (7)

8 USE IN SPECIFIC POPULATIONS

Pediatric use: Safety and effectiveness in pediatric patients have not been established. (8.4)

End-stage Renal Disease with or without Hemodialysis: Not recommended. (8.6)

Severe Hepatic Impairment: Not recommended. (8.7)

FULL PRESCRIBING INFORMATION

1 INDICATIONS AND USAGE

1.1 Overactive Bladder in Adults

GEMTESA® is indicated for the treatment of overactive bladder (OAB) with symptoms of urge urinary incontinence, urgency, and urinary frequency in adults.

1.2 Overactive Bladder in Adult Males with Benign Prostatic Hyperplasia (BPH)

GEMTESA is indicated for the treatment of overactive bladder (OAB) with symptoms of urge urinary incontinence, urgency, and urinary frequency in adult males on pharmacological therapy for benign prostatic hyperplasia (BPH).

2 DOSAGE AND ADMINISTRATION

2.1 Recommended Dosage

The recommended dosage of GEMTESA is one 75 mg tablet orally, once daily with or without food. Swallow GEMTESA tablets whole with a glass of water.

In adults, GEMTESA tablets also may be crushed, mixed with a tablespoon (approximately 15 mL) of applesauce and taken immediately with a glass of water [see Clinical Pharmacology (12.3)].

3 DOSAGE FORMS AND STRENGTHS

Tablets: 75 mg, oval, light green, film-coated, debossed with V75 on one side and no debossing on the other side.

4 CONTRAINDICATIONS

GEMTESA is contraindicated in patients with known hypersensitivity to vibegron or any components of GEMTESA. Hypersensitivity reactions, such as angioedema, have occurred [see Warnings and Precautions (5.2) and Adverse Reactions (6.2)].

5 WARNINGS AND PRECAUTIONS

5.1 Urinary Retention

Urinary retention has been reported in patients taking GEMTESA. The risk of urinary retention may be increased in patients with bladder outlet obstruction and also in patients taking muscarinic antagonist medications for the treatment of OAB. Monitor patients for signs and symptoms of urinary retention, particularly in patients with bladder outlet obstruction or patients taking muscarinic antagonist medications for the treatment of OAB. Discontinue GEMTESA in patients who develop urinary retention [see Adverse Reactions (6.1)].

5.2 Angioedema

Angioedema of the face and/or larynx has been reported with GEMTESA. Angioedema has been reported to occur hours after the first dose or after multiple doses. Angioedema, associated with upper airway swelling, may be life-threatening. If involvement of the tongue, hypopharynx, or larynx occurs, immediately discontinue GEMTESA and provide appropriate therapy and/or measures necessary to ensure a patent airway. GEMTESA is contraindicated in patients with known hypersensitivity to vibegron or any component of GEMTESA [see Contraindications (4) and Adverse Reactions (6.2)].

6 ADVERSE REACTIONS

The following clinically significant adverse reaction is described elsewhere in the labeling:

- Urinary retention [see Warnings and Precautions (5.1)]

6.1 Clinical Trials Experience

Because clinical trials are conducted under widely varying conditions, adverse reaction rates observed in the clinical trials of a drug cannot be directly compared to rates in the clinical trials of another drug and may not reflect the rates observed in practice.

Overactive Bladder in Adults

The safety of GEMTESA was evaluated in a 12-week, double-blind, placebo- and active-controlled study (Study 3003) in patients with OAB [see Clinical Studies (14.1)]. A total of 545 patients received GEMTESA. The majority of the patients were White (78%) and female (85%) with a mean age of 60 years (range 18 to 93 years).

Adverse reactions that were reported in Study 3003 at an incidence greater than placebo and in ≥2% of patients treated with GEMTESA are listed in Table 1.

Table 1: Adverse Reactions, Exceeding Placebo Rate, Reported in ≥2% of Patients Treated with GEMTESA 75 mg for up to 12 Weeks in Study 3003
 | GEMTESA 75 mg n (%) | Placebo n (%)
Number of Patients | 545 | 540
Headache | 22 (4.0) | 13 (2.4)
Nasopharyngitis | 15 (2.8) | 9 (1.7)
Diarrhea | 12 (2.2) | 6 (1.1)
Nausea | 12 (2.2) | 6 (1.1)
Upper respiratory tract infection | 11 (2.0) | 4 (0.7)

Other adverse reactions reported in <2% of patients treated with GEMTESA included:

Gastrointestinal disorders: dry mouth, constipation

Investigations: residual urine volume increased

Renal and urinary disorders: urinary retention

Vascular disorders: hot flush

GEMTESA was also evaluated for long-term safety in an extension study (Study 3004) in 505 patients who completed the 12-week study (Study 3003). Of the 273 patients who received GEMTESA 75 mg once daily in the extension study, 181 patients were treated for a total of one year.

Adverse reactions reported in ≥2% of patients treated with GEMTESA 75 mg for up to 52 weeks in the long-term extension study, and not already listed above, were urinary tract infection (6.6%) and bronchitis (2.9%).

Overactive Bladder in Adult Males with BPH

The safety of GEMTESA was evaluated in a 24-week double-blind, randomized, placebo-controlled study (Study 3005) in male patients with OAB on pharmacological therapy for BPH. A total of 553 patients received GEMTESA [see Clinical Studies (14.2)].

Adverse reactions that were reported in Study 3005 at an incidence greater than placebo and in ≥2% of patients treated with GEMTESA are listed in Table 2.

Table 2: Adverse Reactions, Exceeding Placebo Rate, Reported in ≥2% of Patients Treated with GEMTESA 75 mg for up to 24 Weeks in Study 3005
 | GEMTESA 75 mg n (%) | Placebo n (%)
Number of Patients | 553 | 551
Hypertension* | 50 (9.0) | 46 (8.3)
Urinary tract infection | 14 (2.5) | 12 (2.2)
*Defined as an average systolic blood pressure (SBP) ≥140mmHg or diastolic BP (DBP) ≥90mmHg on 3 assessments at two consecutive visits, in non-hypertensive patients.
*Defined as an average increase of SBP ≥20mmHg or DBP≥10mmHg on 3 assessments at two consecutive visits, or the initiation or increase in dose of antihypertensive medications at any visit, in hypertensive patients.

GEMTESA was also evaluated for long-term safety in a 28-week extension study (Study 3006) in 276 patients who completed the 24-week study (Study 3005). Of the 276 patients who received GEMTESA 75 mg once daily in the extension study, 124 patients were treated for a total of one year.

There were no additional adverse reactions reported in Study 3006 that are not already included in Section 6.1 above.

6.2 Postmarketing Experience

The following adverse reactions have been identified during post-approval use of vibegron. Because these reactions are reported voluntarily from a population of uncertain size, it is not always possible to reliably estimate their frequency or establish a causal relationship to drug exposure. The following adverse events have been reported in association with vibegron use in worldwide postmarketing experience:

Urologic disorders: urinary retention

Skin and subcutaneous tissue disorders: angioedema of the face and larynx; hypersensitivity reactions, including urticaria, pruritus, rash and drug eruption; eczema

Gastrointestinal disorders: constipation

7 DRUG INTERACTIONS

Concomitant use of GEMTESA increases digoxin maximal concentrations (Cmax) and systemic exposure as assessed by area under the concentration-time curve (AUC) [see Clinical Pharmacology (12.3)]. Serum digoxin concentrations should be monitored before initiating and during therapy with GEMTESA and used for titration of the digoxin dose to obtain the desired clinical effect. Continue monitoring digoxin concentrations upon discontinuation of GEMTESA and adjust digoxin dose as needed.

8 USE IN SPECIFIC POPULATIONS

8.1 Pregnancy

Risk Summary

There are no available data on GEMTESA use in pregnant women to evaluate for a drug-associated risk of major birth defects, miscarriage, or adverse maternal or fetal outcomes.

In animal studies, no effects on embryo-fetal development were observed following administration of vibegron during the period of organogenesis at exposures approximately 275-fold and 285-fold greater than clinical exposure at the recommended daily dose of GEMTESA, in rats and rabbits, respectively. Delayed fetal skeletal ossification was observed in rabbits at approximately 898-fold clinical exposure, in the presence of maternal toxicity. In rats treated with vibegron during pregnancy and lactation, no effects on offspring were observed at 89-fold clinical exposure. Developmental toxicity was observed in offspring at approximately 458-fold clinical exposure, in the presence of maternal toxicity. No effects on offspring were observed at 89-fold clinical exposure (see Data).

The background risk of major birth defects and miscarriage for the indicated population is unknown. All pregnancies carry some risk of birth defect, loss, or other adverse outcomes. In the U.S. general population, the estimated background risk of major birth defects and miscarriage in clinically recognized pregnancies is 2-4% and 15-20%, respectively.

Data

Animal Data

In an embryo-fetal developmental toxicity study, pregnant rats were treated with daily oral doses of 0, 30, 100, 300, or 1000 mg/kg/day vibegron during the period of organogenesis (Days 6 to 20 of gestation). These doses were associated with systemic exposures (AUC) 0-, 9-, 89-, 275-, and 1867-fold higher, respectively, than in humans treated with the recommended daily dose of GEMTESA. No embryo-fetal developmental toxicity was observed at doses up to 300 mg/kg/day. Treatment with the high dose of 1000 mg/kg/day was discontinued due to maternal toxicity.

In an embryo-fetal developmental toxicity study, pregnant rabbits were treated with daily oral doses of 0, 30, 100, or 300 mg/kg/day vibegron during the period of organogenesis (Days 7 to 20 of gestation). These doses were associated with systemic exposures (AUC) 0-, 86-, 285-, and 898-fold higher, respectively, than in humans treated with the recommended daily dose of GEMTESA. No embryo-fetal developmental toxicity was observed at doses of vibegron up to 100 mg/kg/day. Maternal toxicity (decreased food consumption), reduced fetal body weight, and an increased incidence of delayed skeletal ossification, were observed at 300 mg/kg/day.

In a pre- and post-natal developmental toxicity study, pregnant or lactating rats were treated with daily oral doses of 0, 30, 100, or 500 mg/kg/day vibegron from day 6 of gestation through day 20 of lactation. These doses were associated with estimated systemic exposures (AUC) 0-, 9-, 89-, and 458-fold higher, respectively, than in humans treated with the recommended daily dose of GEMTESA. No developmental toxicity was observed in F1 offspring at doses up to 100 mg/kg/day. Maternal toxicity was observed during lactation (decreased body weight gain) at doses ≥100 mg/kg/day and during gestation (decreased body weight gain and food consumption) at 500 mg/kg/day. Developmental toxicity was observed in F1 offspring (increased stillborn index, lethality, reduced viability and weaning indices, decreased body weight and body weight gains, low physical development differentiation indices, and effects on sensory function and reflexes) at 500 mg/kg/day.

8.2 Lactation

Risk Summary

There are no data on the presence of vibegron in human milk, the effects of the drug on the breastfed infant, or the effects on milk production. When a single oral dose of radiolabeled vibegron was administered to postnatal nursing rats, radioactivity was observed in milk (see Data). When a drug is present in animal milk, it is likely that the drug will be present in human milk.

The developmental and health benefits of breastfeeding should be considered along with the mother's clinical need for GEMTESA and any potential adverse effects on the breastfed infant from GEMTESA or from the underlying maternal condition.

Data

Animal Data

In a lactational transfer study, lactating rats were treated with a single oral dose of 10 mg/kg radiolabeled [^3H] vibegron on postpartum day 10. Levels of radioactivity were determined in milk and plasma collected at 1, 4, 12, and 24 after dosing. The Cmax of total radioactivity in milk and plasma were observed at 9 and 2 hours after dosing, respectively, with a maximum milk-to-plasma concentration ratio of 2.2 observed at 12 hours after dosing. Vibegron elimination from milk showed a similar trend as that from plasma. The radioactivity concentration in milk at 24 hours after administration was approximately 25% of the Cmax.

8.4 Pediatric Use

The safety and effectiveness of GEMTESA in pediatric patients have not been established.

8.5 Geriatric Use

Of 526 patients who received GEMTESA in the clinical studies for OAB with symptoms of urge urinary incontinence, urgency, and urinary frequency, 242 (46%) were 65 years of age or older, and 75 (14%) were 75 years of age or older [see Clinical Studies (14.1)]. No overall differences in safety or effectiveness of GEMTESA have been observed between patients 65 years of age and older and younger adult patients.

Of the total number of GEMTESA-treated patients in clinical studies for OAB with symptoms of urge urinary incontinence, urgency, and urinary frequency in adult males on pharmacological therapy for benign prostatic hyperplasia (BPH), 347 (63%) were 65 years of age and older, while 100 (18%) were 75 years of age and older [see Clinical Studies (14.2)]. No overall differences in safety of GEMTESA have been observed between patients 65 years of age and older and younger adult patients.

8.6 Renal Impairment

No dosage adjustment for GEMTESA is recommended for patients with mild, moderate, or severe renal impairment (eGFR 15 to <90 mL/min/1.73 m^2). GEMTESA has not been studied in patients with eGFR <15 mL/min/1.73 m^2 (with or without hemodialysis) and is not recommended in these patients [see Clinical Pharmacology (12.3)].

8.7 Hepatic Impairment

No dosage adjustment for GEMTESA is recommended for patients with mild to moderate hepatic impairment (Child-Pugh A and B). GEMTESA has not been studied in patients with severe hepatic impairment (Child-Pugh C) and is not recommended in this patient population [see Clinical Pharmacology (12.3)].

10 OVERDOSAGE

There is no experience with inadvertent GEMTESA overdosage. In case of suspected overdose, treatment should be symptomatic and supportive.

11 DESCRIPTION

Vibegron is a selective beta-3 adrenergic agonist. The chemical name is (6S)-N-[4-[[(2S,5R)-5-[(R)-hydroxy(phenyl)methyl]pyrrolidin-2-yl]methyl]phenyl]-4-oxo-7,8-dihydro-6H-pyrrolo[1,2-a]pyrimidine-6-carboxamide having a molecular formula of C26H28N4O3 and a molecular weight of 444.538 g/mol. The structural formula of vibegron is:

Vibegron is a crystalline, white to off-white to tan powder.

GEMTESA tablets, for oral administration contain 75 mg of vibegron and the following inactive ingredients: croscarmellose sodium, hydroxypropyl cellulose, magnesium stearate, mannitol, and microcrystalline cellulose. The light green film coating contains FD&C Blue No. 2 - aluminum lake, hypromellose, iron oxide yellow, lactose monohydrate, titanium dioxide, and triacetin.

12 CLINICAL PHARMACOLOGY

12.1 Mechanism of Action

Vibegron is a selective human beta-3 adrenergic receptor agonist. Activation of the beta-3 adrenergic receptor increases bladder capacity by relaxing the detrusor smooth muscle during bladder filling.

12.2 Pharmacodynamics

Vibegron's exposure-response relationship and the time course of pharmacodynamic response are not fully characterized.

Blood Pressure

In a 4-week, randomized, placebo-controlled, ambulatory blood pressure study in OAB patients (n=200), daily treatment with GEMTESA 75 mg was not associated with clinically significant changes in blood pressure. Subjects enrolled in this study had a mean age of 59 years and 75% were female. Thirty-five percent of subjects had pre-existing hypertension at baseline and 29% of all subjects were taking at least 1 concomitant antihypertensive medication.

Cardiac Electrophysiology

GEMTESA does not prolong the QT interval to any clinically relevant extent at a single dose 5.3 times the approved recommended dose.

12.3 Pharmacokinetics

Mean vibegron Cmax and AUC increased in a greater than dose-proportional manner up to 600 mg (8 times the approved recommended dosage). Steady state concentrations are achieved within 7 days of once daily dosing. The mean accumulation ratio (Rac) was 1.7 for Cmax and 2.4 for AUC0-24hr.

Absorption

Median vibegron Tmax is approximately 1 to 3 hours.

Oral administration of a 75 mg vibegron tablet crushed and mixed with 15 mL of applesauce resulted in no clinically relevant changes in vibegron pharmacokinetics when compared to administration of an intact 75 mg vibegron tablet.

Effect of Food

No clinically significant differences in vibegron pharmacokinetics were observed following administration of a high-fat meal (53% fat, 869 calories [32.1 g protein, 70.2 g carbohydrate, and 51.1 g fat]).

Distribution

The mean apparent volume of distribution is 6304 liters. Human plasma protein binding of vibegron is approximately 50%. The average blood-to-plasma concentration ratio is 0.9.

Elimination

Vibegron has an effective half-life of 30.8 hours across all populations.

Metabolism

Metabolism plays a minor role in the elimination of vibegron. CYP3A4 is the predominant enzyme responsible for in vitro metabolism.

Excretion

Following a radiolabeled dose, approximately 59% of the dose (54% as unchanged) was recovered in feces and 20% (19% as unchanged) in urine.

Specific Populations

No clinically significant differences in the pharmacokinetics of vibegron were observed based on age (18 to 93 years), sex, race/ethnicity (Japanese vs. non-Japanese), mild (eGFR 60 to <90 mL/min/1.73 m^2), moderate (eGFR 30 to <60 mL/min/1.73 m^2), and severe (eGFR 15 to <30 mL/min/1.73 m^2) renal impairment, or moderate (Child-Pugh B) hepatic impairment. The effect of more severe renal impairment (eGFR <15 mL/min/1.73 m^2) with or without hemodialysis or severe (Child-Pugh C) hepatic impairment on vibegron pharmacokinetics was not studied.

Drug Interaction Studies

Clinical Studies

Digoxin: Concomitant administration of vibegron increased digoxin Cmax and AUC by 21% and 11%, respectively.

Other Drugs: No clinically significant differences in vibegron pharmacokinetics were observed when used concomitantly with ketoconazole (P-gp and strong CYP3A4 inhibitor), diltiazem (P-gp and moderate CYP3A4 inhibitor), rifampin (strong CYP3A4 inducer), or tolterodine. No clinically significant differences in the pharmacokinetics of the following drugs were observed when used concomitantly with vibegron: tolterodine, tolterodine 5-hydroxy metabolite, metoprolol, combined oral contraceptive (ethinyl estradiol, levonorgestrel), or warfarin.

In Vitro Studies

Cytochrome P450 (CYP) Enzymes: Vibegron is a CYP3A4 substrate. Vibegron did not inhibit CYP1A2, CYP2B6, CYP2C8, CYP2C9, CYP2C19, CYP2D6, or CYP3A4. Vibegron did not induce CYP1A2, CYP2B6, or CYP3A4.

Transporter Systems: Vibegron is a P-gp substrate. Vibegron did not inhibit P-gp, BCRP, OATP1B1, OATP1B3, OAT1, OAT3, OCT1, OCT2, MATE1, or MATE2K at clinically relevant concentrations.

13 NONCLINICAL TOXICOLOGY

13.1 Carcinogenesis, Mutagenesis, Impairment of Fertility

Carcinogenesis

No carcinogenicity was observed in long-term studies conducted in mice and rats treated with daily oral doses of vibegron for approximately 2 years. In the mouse carcinogenicity study, CD-1 mice were treated with daily oral doses of vibegron up to 90 mg/kg/day in males and up to 150 mg/kg/day in females, corresponding to estimated systemic exposures (AUC) 21- and 55-fold higher, respectively, than in humans treated with the recommended daily dose of GEMTESA. In the rat carcinogenicity study, Sprague Dawley rats were treated with daily oral doses of vibegron up to 30 mg/kg/day in males and up to 180 mg/kg/day in females, corresponding to systemic exposures (AUC) 18- and 117-fold higher, respectively, than in humans treated with the recommended daily dose of GEMTESA.

Mutagenesis

Vibegron was not mutagenic in in vitro microbial reverse mutation assays, showed no evidence of genotoxic activity in an in vitro human peripheral blood lymphocyte chromosomal aberration assay, and did not increase the frequency of micronucleated polychromatic erythrocytes in an in vivo rat bone marrow micronucleus assay.

Impairment of Fertility

In fertility/general reproductive toxicity studies conducted in rats, females were treated with daily oral doses of 0, 30, 100, 300, or 1000 mg/kg/day vibegron and males were treated with daily oral doses of 0, 10, 30, or 300 mg/kg/day vibegron. No effects on fertility were observed in female or male rats at doses up to 300 mg/kg/day, associated with systemic exposure (AUC) at least 274-fold higher than in humans treated with the recommended daily dose of GEMTESA. General toxicity, decreased fecundity, and decreased fertility were observed in female rats at 1000 mg/kg/day, associated with estimated systemic exposure 1867-fold higher than in humans treated with the recommended daily dose of GEMTESA.

14 CLINICAL STUDIES

14.1 Overactive Bladder in Adults

The efficacy of GEMTESA was evaluated in a 12-week, double-blind, randomized, placebo-controlled, and active-controlled trial (Study 3003, NCT03492281) in patients with OAB (urge urinary incontinence, urgency, and urinary frequency). Patients were randomized 5:5:4 to receive either GEMTESA 75 mg, placebo, or active control orally, once daily for 12 weeks. For study entry, patients had to have symptoms of OAB for at least 3 months with an average of 8 or more micturitions per day and at least 1 urge urinary incontinence (UUI) per day, or an average of 8 or more micturitions per day and an average of at least 3 urgency episodes per day. Urge urinary incontinence was defined as leakage of urine of any amount because the patient felt an urge or need to urinate immediately. The study population included OAB medication-naïve patients as well as patients who had received prior therapy with OAB medications.

The co-primary endpoints were change from baseline in average daily number of micturitions and average daily number of UUI episodes at week 12. Additional endpoints included change from baseline in average daily number of “need to urinate immediately” (urgency) episodes and average volume voided per micturition.

A total of 1,515 patients received at least one daily dose of placebo (n=540), GEMTESA 75 mg (n=545), or an active control treatment (n=430). The majority of patients were White (78%) and female (85%) with a mean age of 60 (range 18 to 93) years.

Table 3 shows changes from baseline at week 12 for average daily number of micturitions, average daily number of UUI episodes, average daily number of “need to urinate immediately” (urgency) episodes, and average volume voided per micturition.

Table 3: Mean Baseline and Change from Baseline at Week 12 for Micturition Frequency, Urge Urinary Incontinence Episodes, "Need to Urinate Immediately" (Urgency) Episodes, and Volume Voided per Micturition
Parameter | GEMTESA 75 mg | Placebo
Average Daily Number of Micturitions
Baseline mean (n) | 11.3 (526) | 11.8 (520)
Change from Baseline* (n) | -1.8 (492) | -1.3 (475)
Difference from Placebo | -0.5
95% Confidence Interval | -0.8, -0.2
p-value | <0.001
Average Daily Number of UUI Episodes
Baseline mean (n) | 3.4 (403) | 3.5 (405)
Change from Baseline* (n) | -2.0 (383) | -1.4 (372)
Difference from Placebo | -0.6
95% Confidence Interval | -0.9, -0.3
p-value | <0.0001
Average Daily Number of “Need to Urinate Immediately” (Urgency) Episodes
Baseline mean (n) | 8.1 (526) | 8.1 (520)
Change from Baseline* (n) | -2.7 (492) | -2.0 (475)
Difference from Placebo | -0.7
95% Confidence Interval | -1.1, -0.2
p-value | 0.002
Average Volume Voided (mL) per Micturition
Baseline mean (n) | 155 (524) | 148 (514)
Change from Baseline* (n) | 23 (490) | 2 (478)
Difference from Placebo | 21
95% Confidence Interval | 14, 28
p-value | <0.0001
* Least squares mean adjusted for treatment, baseline, sex, geographical region, study visit, and study visit by treatment interaction term.

Figure 1 and Figure 2 show the mean change from baseline over time in average daily number of micturitions and mean change from baseline over time in average daily number of UUI episodes, respectively.

Figure 1: Mean (SE) Change from Baseline in the Average Daily Number of Micturitions

Figure 2: Mean (SE) Change from Baseline in the Average Daily Number of UUI Episodes in Patients with At Least 1 Average Daily UUI Episode at Baseline

14.2 Overactive Bladder in Adult Males with BPH

The safety, tolerability, and efficacy of GEMTESA was evaluated in a multinational 24-week, double-blind, randomized, placebo-controlled trial (Study 3005, NCT03902080) in male patients at least 45 years of age with OAB on pharmacological therapy (i.e., treatment with an alpha blocker, with or without a 5-alpha reductase inhibitor) for BPH. A total of 1105 patients were randomized 1:1 to receive either GEMTESA 75 mg or placebo once daily for 24 weeks. For study entry, patients had symptoms of OAB (an average of 8 or more micturitions per day, 3 or more urgency episodes per day with or without incontinence, and 2 or more nocturia episodes per night) while taking pharmacological therapy for at least 2 months for the treatment of lower urinary tract symptoms due to BPH. Randomization was stratified based on the baseline average number of micturition episodes per day, alpha blocker use with or without 5 alpha reductase inhibitor use, and urinary incontinence.

The co-primary endpoints were change from baseline in the average daily number of micturitions and the average daily number of “need to urinate immediately” (urgency) episodes at week 12. Additional endpoints included change from baseline in the average daily number of urge urinary incontinence (UUI) episodes and the average volume voided per micturition.

A total of 1104 patients received at least one daily dose of placebo (n=551) or GEMTESA 75 mg (n=553). The majority of patients were White (87%) and enrolled in the U.S. (56%). The mean age was 67 years (range 45 to 97) and at least 63% were ≥ 65 years.

Table 4 shows changes from baseline at week 12 for average daily number of micturitions, average daily number of urgency episodes, average daily number of UUI episodes and average volume voided per micturition.

Table 4: Mean Baseline and Change from Baseline at Week 12 for Micturition Frequency, "Need to Urinate Immediately" (Urgency Episodes), UUI Episodes and Volume Voided per Micturition
Parameter | GEMTESA 75 mg (N = 538) | Placebo (N = 542)
Average Daily Number of Micturitions
Baseline mean | 11.84 | 11.96
Change from Baseline* | -2.04 | -1.30
Difference from Placebo | -0.74
95% Confidence Interval | -1.02, -0.46
Average Daily Number of “Need to Urinate Immediately” (Urgency) Episodes
Baseline mean | 9.05 | 9.00
Change from Baseline* | -2.88 | -1.93
Difference from Placebo | -0.95
95% Confidence Interval | -1.37, -0.54
Average Daily Number of UUI Episodes
N *** | 146 | 151
Baseline mean | 3.33 | 3.23
Change from Baseline* | -2.19 | -1.39
Difference from Placebo | -0.80
95% Confidence Interval | -1.33, -0.27
Average Volume Voided (mL) per Micturition
Baseline mean | 166.37 | 166.43
Change from Baseline* | 25.63 | 10.56
Difference from Placebo | 15.07
95% Confidence Interval | 9.13, 21.02
* Least squares mean adjusted for study visit, baseline value, geographical region, interaction of visit by treatment, and stratification factors as randomized (baseline average micturitions per day**, alpha blocker use with or without 5-ARI, baseline urinary incontinence**), geographical region, study visit, and study visit by treatment interaction term.
** Baseline average micturitions per day stratification factor is not included in the model where the continuous value of baseline average micturitions per day is present; baseline urinary incontinence is not included in the model for UUI;
*** Only subjects with baseline incontinence have UUI analyzed.

Figure 3 and Figure 4 show the mean change from baseline over time in average daily number of micturitions and mean change from baseline over time in average daily number of urgency episodes, respectively.

Figure 3: Mean (SE) Change from Baseline in the Average Daily Number of Micturitions in Male Patients with BPH on Pharmacological Therapy

Figure 4: Mean (SE) Change from Baseline in the Average Daily Number of Urgency Episodes in Male Patients with BPH on Pharmacological Therapy

16 HOW SUPPLIED/STORAGE AND HANDLING

GEMTESA 75 mg tablets are light green, oval, film-coated tablets, debossed with V75 on one side and no debossing on the other side.

GEMTESA is marketed in two packaging configurations:

Thirty (30) tablets in a HDPE bottle with a child-resistant cap, NDC 73336-075-30

Ninety (90) tablets in a HDPE bottle with a child-resistant cap, NDC 73336-075-90

Store at 20°C to 25°C (68°F to 77°F), excursions permitted to 15°C to 30°C (59°F to 86°F) [see USP Controlled Room Temperature].

Keep this and all medications out of sight and reach of children.

Dispose unused medication via a take-back option if available; otherwise follow FDA instructions for disposal in the household trash. See www.fda.gov/drugdisposal for more information.

17 PATIENT COUNSELING INFORMATION

Advise the patient to read the FDA-approved patient labeling (Patient Information).

Urinary Retention

Inform patients that GEMTESA has been associated with urinary retention. Inform patients that the risk of urinary retention may be increased in patients taking muscarinic antagonist medications for the treatment of OAB. Instruct patients to contact their healthcare provider if they experience symptoms consistent with urinary retention while taking GEMTESA [see Warnings and Precautions (5.1)].

Angioedema

Inform patients that GEMTESA may cause angioedema. Advise patients to immediately discontinue GEMTESA and seek medical attention if angioedema associated with upper airway swelling occurs as this may be life-threatening [see Contraindications (4) and Warnings and Precautions (5.2)].

Administration Instructions

Advise patients that GEMTESA tablets can be swallowed whole with a glass of water or may be crushed, mixed with a tablespoon of applesauce and taken immediately with a glass of water [see Dosage and Administration (2.1)].

Manufactured for and Distributed by:
Sumitomo Pharma America, Inc.
Marlborough, MA 01752

is a trademark of Sumitomo Pharma Co., Ltd., used under license.

SUMITOMO PHARMA is a trademark of Sumitomo Pharma Co., Ltd., used under license.

SUMITOMO is a registered trademark of Sumitomo Chemical Co., Ltd., used under license.

Sumitomo Pharma America, Inc. is a U.S. subsidiary of Sumitomo Pharma Co., Ltd.

All other trademarks are the property of their respective owners.

PATIENT INFORMATION
GEMTESA [gem tes' ah]
(vibegron)
tablets, for oral use

What is GEMTESA?
GEMTESA is a prescription medicine used to treat the following symptoms due to a condition called overactive bladder in adults, and in adult males taking medicine for benign prostatic hyperplasia (BPH):

- urge urinary incontinence: a strong need to urinate with leaking or wetting accidents
- urgency: the need to urinate right away
- frequency: urinating often

It is not known if GEMTESA is safe and effective in children.

Do not take GEMTESA if you:

- are allergic to vibegron or any of the ingredients in GEMTESA. See the end of this leaflet for a complete list of ingredients in GEMTESA.

Before you take GEMTESA, tell your doctor about all of your medical conditions, including if you:
have liver problems.

- have kidney problems.
- have trouble emptying your bladder or you have a weak urine stream.
- take medicines that contain digoxin.
- are pregnant or plan to become pregnant. It is not known if GEMTESA will harm your unborn baby. Talk to your doctor if you are pregnant or plan to become pregnant.
- are breastfeeding or plan to breastfeed. It is not known if GEMTESA passes into your breast milk. Talk to your doctor about the best way to feed your baby if you take GEMTESA.

Tell your doctor about all the medicines you take, including prescription and over-the-counter medicines, vitamins, and herbal supplements.
Know the medicines you take. Keep a list of them to show your doctor and pharmacist when you get a new medicine.

How should I take GEMTESA?

- Take GEMTESA exactly as your doctor tells you to take it.
- Take 1 GEMTESA tablet, by mouth, 1 time a day with or without food.
- Swallow GEMTESA tablets whole with a glass of water.
- You may also crush GEMTESA tablets, mix with 1 tablespoon (about 15 mL) of applesauce, and take right away with a glass of water.

What are the possible side effects of GEMTESA?
GEMTESA may cause serious side effects, including:

- inability to empty your bladder (urinary retention). GEMTESA may increase your chances of not being able to empty your bladder, especially if you have bladder outlet obstruction or take other medicines for treatment of overactive bladder. Tell your doctor right away if you are unable to empty your bladder.
- angioedema. GEMTESA may cause an allergic reaction with swelling of the lips, face, tongue, or throat, with or without difficulty breathing and may be life-threatening. Stop using GEMTESA and get emergency medical help right away if you have symptoms of angioedema or trouble breathing.

The most common side effects of GEMTESA include:

- urinary tract infection
- headache

- nasal congestion, sore throat or runny nose
- diarrhea

- nausea
- upper respiratory tract infection

These are not all the possible side effects of GEMTESA. For more information, ask your doctor or pharmacist.
Call your doctor for medical advice about side effects. You may report side effects to FDA at 1-800-FDA-1088.

How should I store GEMTESA?

- Store GEMTESA at room temperature between 68°F to 77°F (20°C to 25°C).
- Safely throw away medicine that is no longer needed in your household trash.
- You may also dispose of the unused medicine through a take-back option, if available. See www.fda.gov/drugdisposal for more information.

Keep GEMTESA and all medicines out of the reach of children.

General information about the safe and effective use of GEMTESA.
Medicines are sometimes prescribed for purposes other than those listed in a Patient Information leaflet. Do not use GEMTESA for a condition for which it was not prescribed. Do not give GEMTESA to other people, even if they have the same symptoms that you have. It may harm them.
You can ask your doctor or pharmacist for information about GEMTESA that is written for health professionals.

What are the ingredients in GEMTESA?
Active ingredient: vibegron
Inactive ingredients: croscarmellose sodium, hydroxypropyl cellulose, magnesium stearate, mannitol, and microcrystalline cellulose. The light green film coating contains FD&C Blue No. 2 - aluminum lake, hypromellose, iron oxide yellow, lactose monohydrate, titanium dioxide, and triacetin.

Manufactured for and Distributed by:
Sumitomo Pharma America, Inc.
Marlborough, MA 01752
is a trademark of Sumitomo Pharma Co., Ltd., used under license.
SUMITOMO PHARMA is a trademark of Sumitomo Pharma Co., Ltd., used under license.
SUMITOMO is a registered trademark of Sumitomo Chemical Co., Ltd., used under license.
Sumitomo Pharma America, Inc. is a U.S. subsidiary of Sumitomo Pharma Co., Ltd.
All other trademarks are the property of their respective owners.
For more information, go to www.GEMTESA.com or call 1-833-876-8268.

This Patient Information has been approved by the U.S. Food and Drug Administration.

Approved: 12/2024

PRINCIPAL DISPLAY PANEL - 75 mg Tablet Bottle Label

30 tablets

NDC 73336-075-30

Rx Only

GEMTESA®
(vibegron) tablets

75 mg

One Tablet • Once Daily
May be swallowed whole or crushed